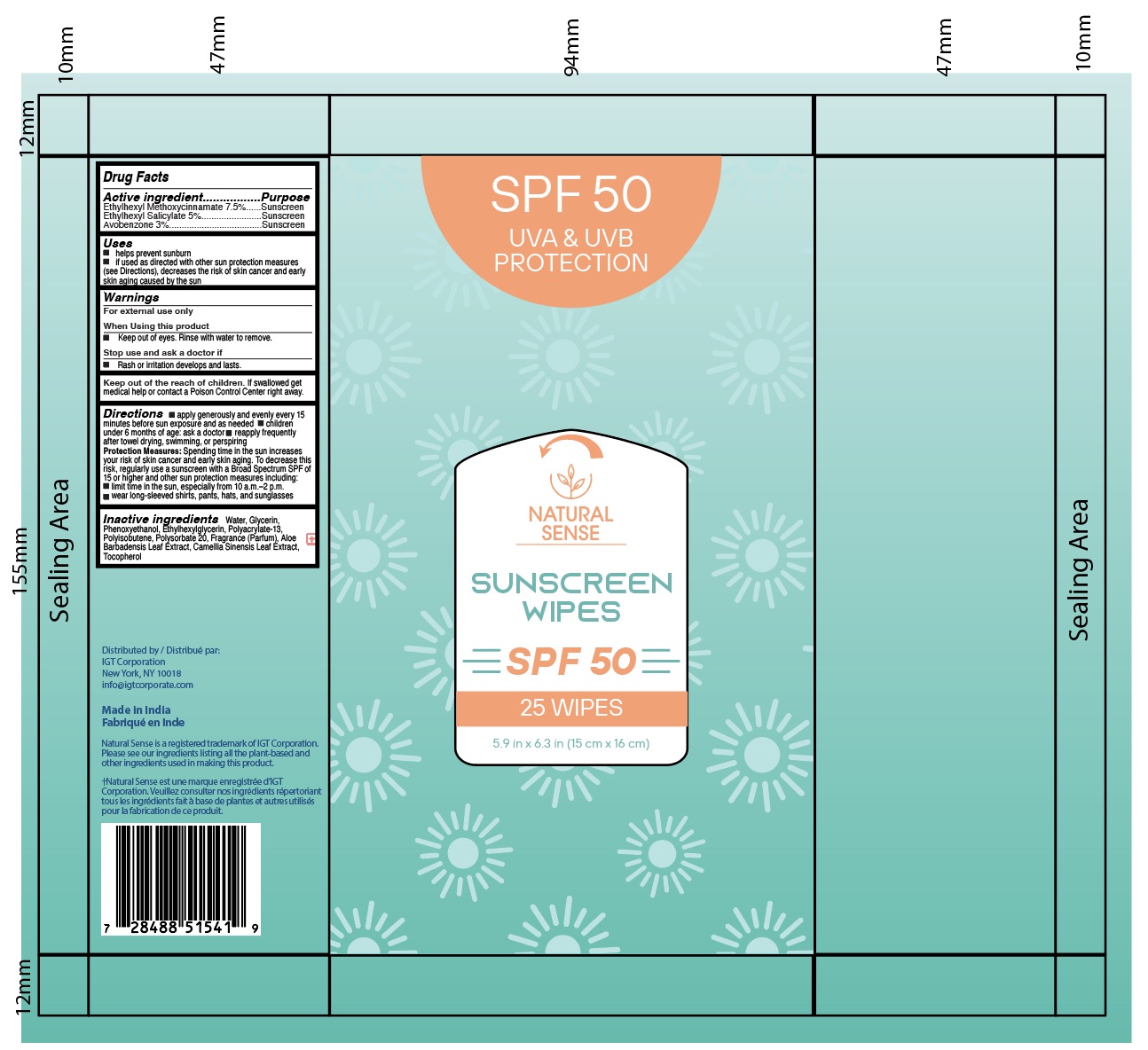 DRUG LABEL: Natural Sense SPF 50 Sunscreen
NDC: 78261-324 | Form: CLOTH
Manufacturer: Dr. Natural LLC
Category: otc | Type: HUMAN OTC DRUG LABEL
Date: 20260130

ACTIVE INGREDIENTS: OCTINOXATE 5 g/100 g; AVOBENZONE 3 g/100 g; OCTISALATE 3 g/100 g; OCTOCRYLENE 6 g/100 g
INACTIVE INGREDIENTS: ALOE BARBADENSIS LEAF JUICE; FRAGRANCE 13576; CAMELLIA SINENSIS LEAF OIL; GLYCERIN; VITAMIN E POLYETHYLENE GLYCOL SUCCINATE; POLYACRYLATE-13; PHENOXYETHANOL; WATER

PURPOSE

Sunscreen

Active ingredients
Octinoxate 5% .................................. Sunscreen
Octisalate 3% .................................. Sunscreen
Avobenzone 3% .................................. Sunscreen
Octocrylene 6% ................................ Sunscreen

When using this product keep out of eyes. Rinse with water to remove.

Stop use and ask a doctor if rash occurs.

Keep out of reach of children. If swallowed, get medical help or contact a Poison Control Center right away.

Do not use on damaged or broken skin.

INDICATIONS AND USAGE

Helps prevent sunburn.
If used as directed with other sun protection measures (see Directions),
decreases the risk of skin cancer and early skin aging caused by the sun.

DOSAGE AND ADMINISTRATION

Apply liberally and evenly 15 minutes before sun exposure.
Reapply at least every 2 hours.
Use a water resistant sunscreen if swimming or sweating.
Children under 6 months of age: ask a doctor.

WARNINGS

For external use only.
Do not use on damaged or broken skin.
When using this product keep out of eyes. Rinse with water to remove.
Stop use and ask a doctor if rash occurs.
Keep out of reach of children. If swallowed, get medical help or contact a Poison Control Center right away.

INACTIVE INGREDIENT

Water, Glycerin, Phenoxyethanol, Ethylhexylglycerin, Polyacrylate-13,
Polyisobutene, Polysorbate 20, Fragrance, Aloe Barbadensis Leaf Extract,
Camellia Sinensis Leaf Extract, Tocopherol